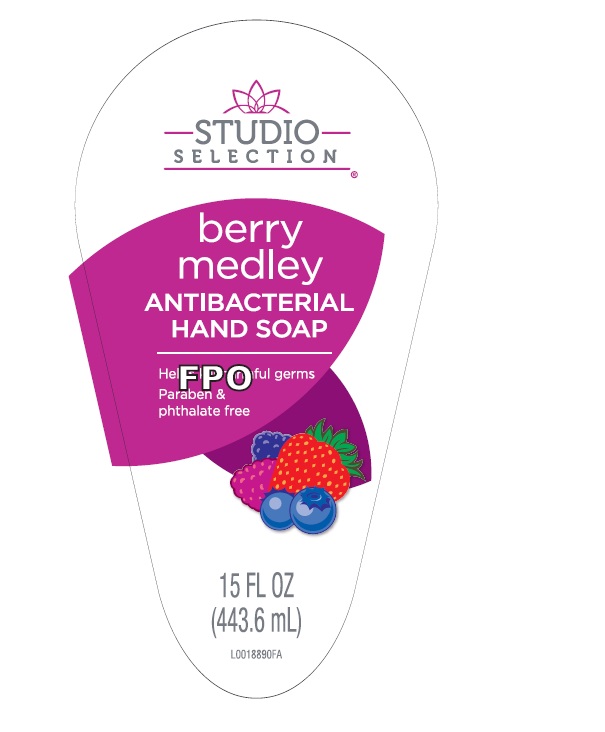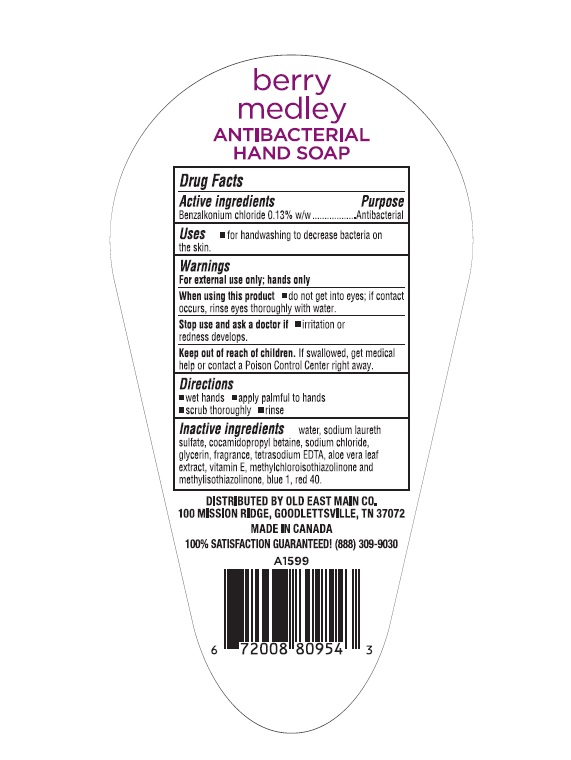 DRUG LABEL: Antibacterial
NDC: 50157-608 | Form: LIQUID
Manufacturer: Brands International Corporation
Category: otc | Type: HUMAN OTC DRUG LABEL
Date: 20221114

ACTIVE INGREDIENTS: BENZALKONIUM CHLORIDE 1.3 mg/1000 mL
INACTIVE INGREDIENTS: .ALPHA.-TOCOPHEROL ACETATE, D-; ALOE VERA LEAF; FD&C BLUE NO. 1; FD&C RED NO. 40; SODIUM CHLORIDE; EDETATE SODIUM; METHYLCHLOROISOTHIAZOLINONE; WATER; SODIUM LAURETH SULFATE; COCAMIDOPROPYL BETAINE; METHYLISOTHIAZOLINONE

Studio selection Antibacterial liquid hand soap- Berry medley

Active Ingredient - Benzalkonium Chloride - 0.13%

Purpose - Antibacterial

INDICATIONS AND USAGE

Use for handwashing to decrease bacteria on skin

WARNINGS

for external use only - hands only

When using this product avoid contact with eyes. If contact occurs, rinse eyes thoroughly with water

Stop use and ask a doctor if irritation or redness develops.

keep out of reach of children. If swallowed, get medical help or contact a Poison Control Center immediately

DOSAGE AND ADMINISTRATION

Direction

* wet hands

* apply to hands

* scrub thoroughly

* rinse thoroughly

INACTIVE INGREDIENT

Water, Sodium Laureth Sulfate, Cocamidopropyl Betaine, Sodium Chloride, Glycerin, Tetrasodium EDTA, Methylchloroisothiazolinone, Methylisothiazolinone, Vitamin E, Blue# 1, Yellow 5, Fragrance (Parfum)